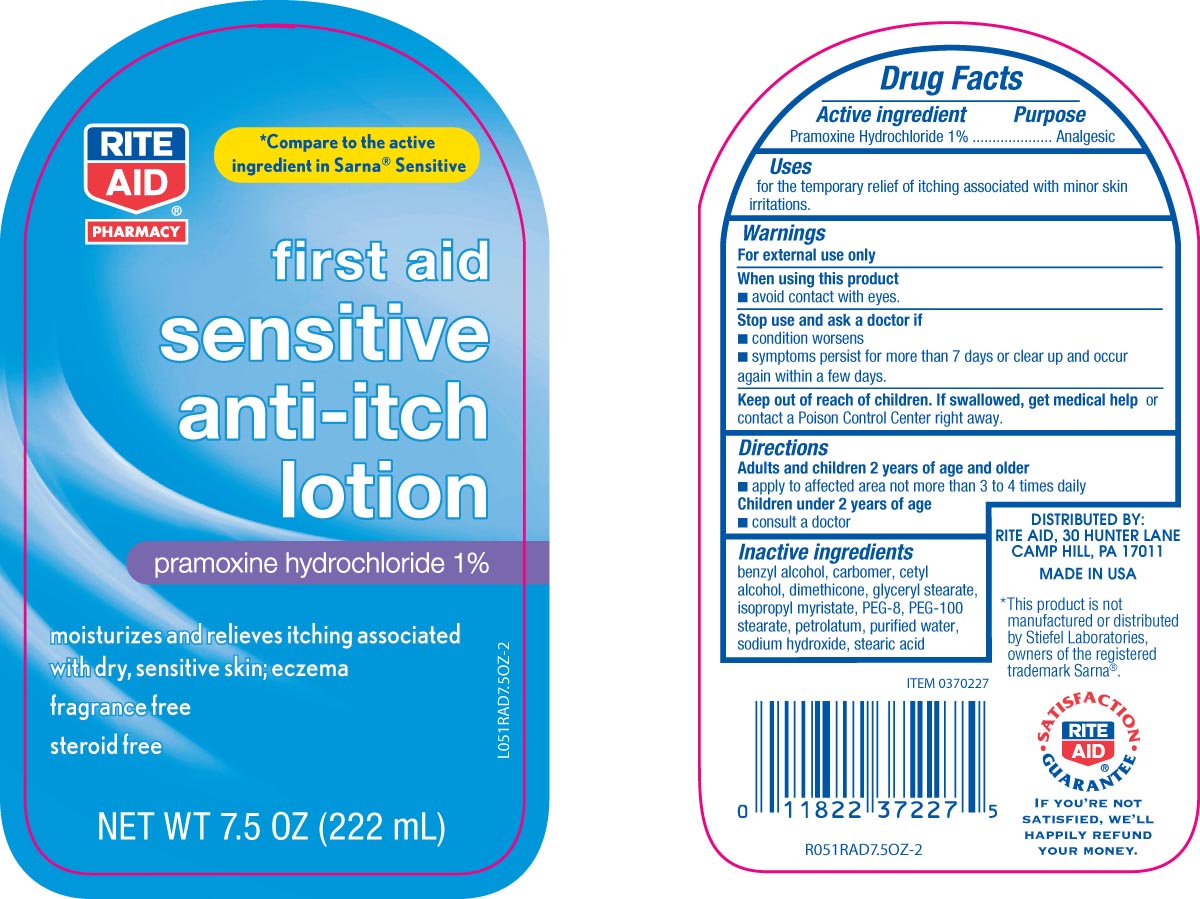 DRUG LABEL: CVS Fragrance Free Anti-Itch
NDC: 11822-0405 | Form: LOTION
Manufacturer: RITE AID CORPORATION
Category: otc | Type: HUMAN OTC DRUG LABEL
Date: 20100708

ACTIVE INGREDIENTS: PRAMOXINE HYDROCHLORIDE 10 mg/1 mL
INACTIVE INGREDIENTS: WATER; CARBOMER HOMOPOLYMER TYPE C; ISOPROPYL MYRISTATE; GLYCERYL MONOSTEARATE; STEARIC ACID; CETYL ALCOHOL; PETROLATUM; DIMETHICONE 350; POLYETHYLENE GLYCOL 400; BENZYL ALCOHOL; SODIUM HYDROXIDE; POLYETHYLENE GLYCOL 4500

DRUG FACTS

Active ingredient Purpose
Pramoxine Hydrochloride 1%............................External Analgesic

Uses
For the temporary relief of itching associated with minor skin irritations

Keep out of reach of children. If swallowed, get medical help or contact a
Poison Control Center right away.

Uses
For the temporary relief of itching associated with minor skin irritations

Warnings
For external use only
When using this product
- avoid contact with eyes
Stop use and ask a doctor if
- condition worsens
- symptoms persist for more than 7 days or clear up and occur again within a few days.
Keep out of reach of children.If swallowed, get medical help or contact a
Poison Control Center right away.

Directions
adults and children 2 years and older
- apply to affected area not more than 3 to 4 times daily
children under 2 years of age
- consult a doctor

Inactive Ingredients
benzyl alcohol, carbomer, cetyl alcohol, dimethicone, glycerul stearate, isopropyl myristate,
PEG-8, PEG-100 stearate, petrolatum, purified water, sodium hydroxide, stearic acid